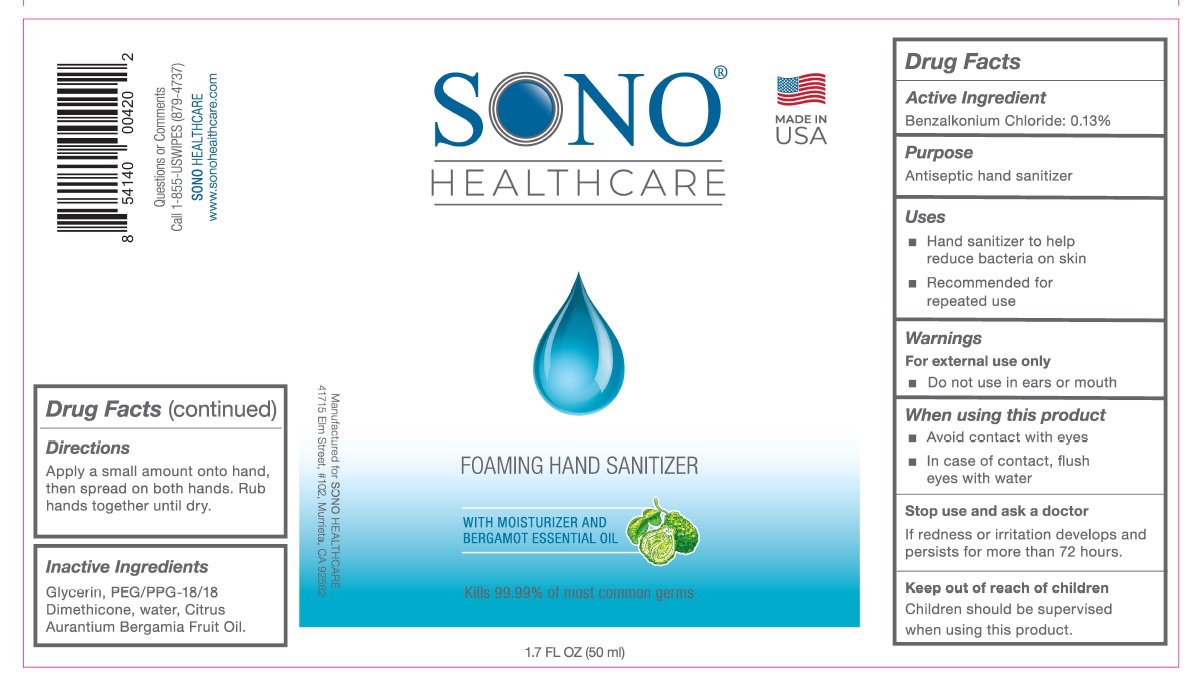 DRUG LABEL: SONO Hand Sanitizer
NDC: 77677-001 | Form: SOLUTION
Manufacturer: Advanced Ultrasound Solutions Inc.
Category: otc | Type: HUMAN OTC DRUG LABEL
Date: 20231214

ACTIVE INGREDIENTS: BENZALKONIUM CHLORIDE 0.13 g/100 g
INACTIVE INGREDIENTS: GLYCERIN; PEG/PPG-18/18 DIMETHICONE; WATER; BERGAMOT OIL

SONO Foaming Hand Sanitizer

Active Ingredient

Benzalkonium chloride.........0.13%

Purpose

Antiseptic Hand Sanitizer

Uses

- Hand sanitizer to help reduce bacteria on skin
- Recommended for repeated use

Warnings

For external use only

Do not use in ears or mouth

When using this product

Avoid contact with eyes. In case of contact, flush eyes with water.

Stop use and ask a doctor

If redness or irritation develops and persists for more than 72 hours.

Keep out of reach of children

Children should be supervised when using this product

Directions

- Apply a small amount onto hand, then spread on both hands
- Rub hands together until dry

Inactive ingredients

Glycerin, PEG/PPG-18/18 Dimethicone, water, Organic Citrus Aurantium Bergamia Fruit Oil.